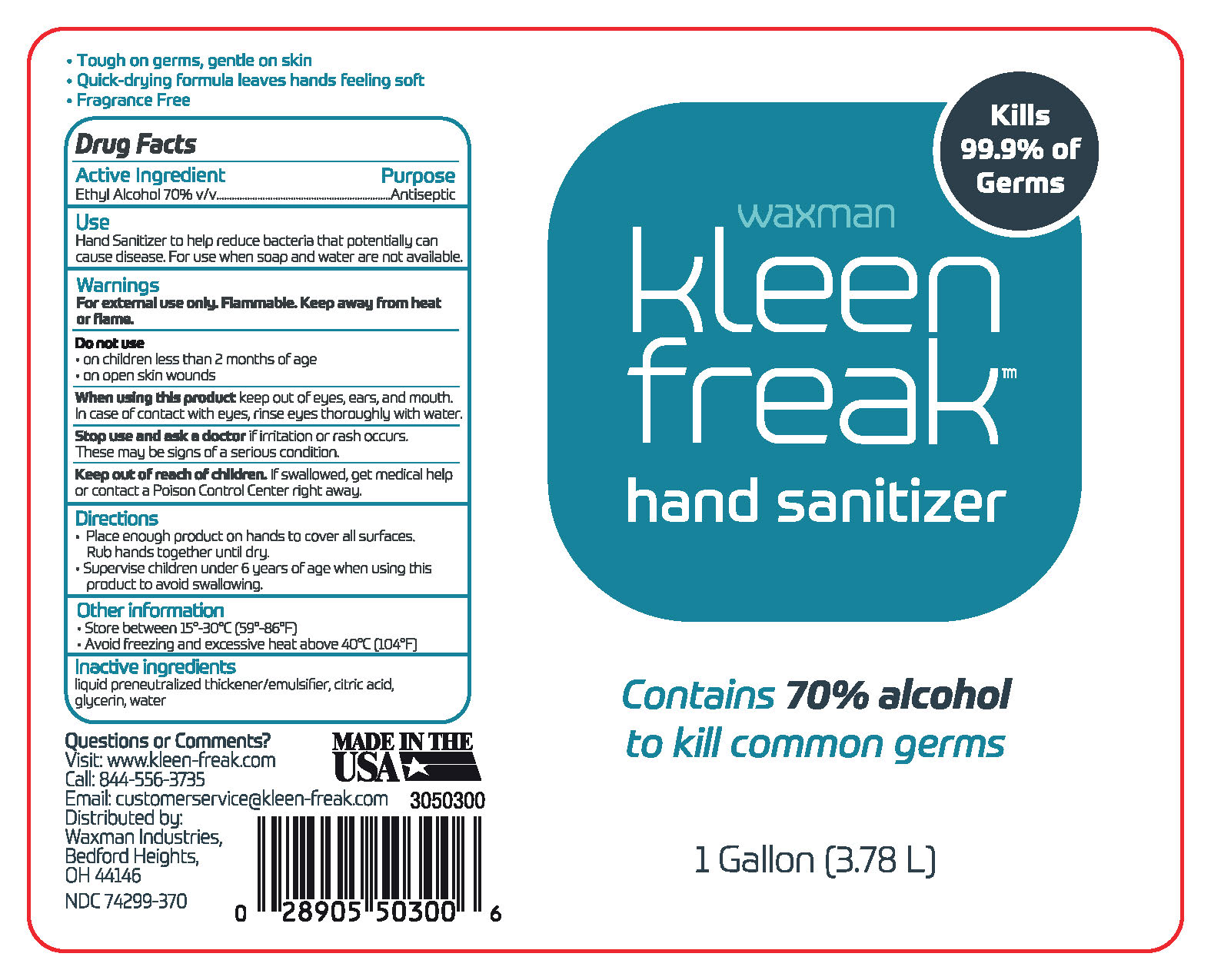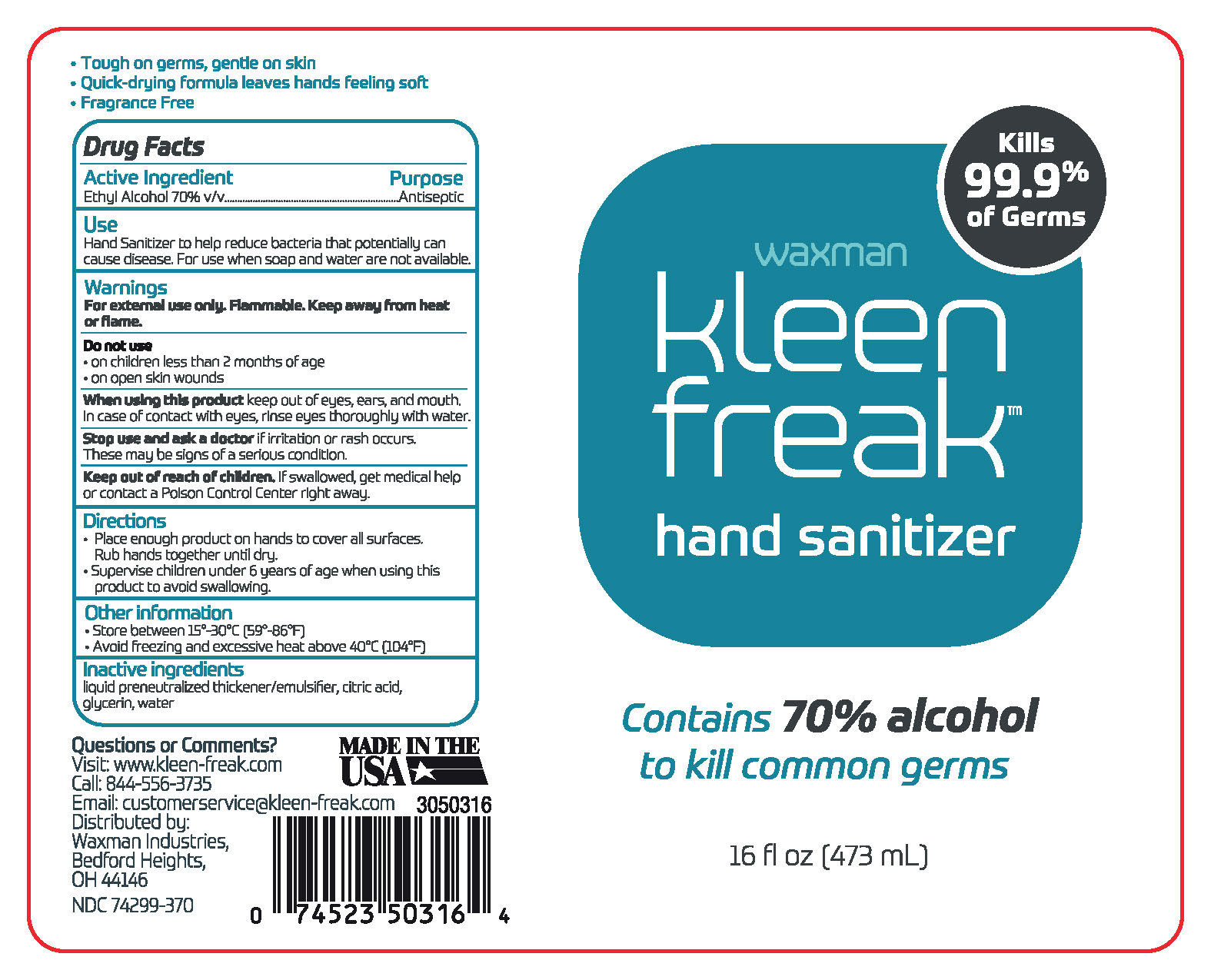 DRUG LABEL: Waxman Kleen Freak Hand Sanitizer
NDC: 74299-370 | Form: LIQUID
Manufacturer: Southern Distilling Company, LLC
Category: otc | Type: HUMAN OTC DRUG LABEL
Date: 20200901

ACTIVE INGREDIENTS: ALCOHOL 0.62 mL/1 mL
INACTIVE INGREDIENTS: WATER; ANHYDROUS CITRIC ACID; GLYCERIN; RAPIDGEL EZ1

ACTIVE INGREDIENT

Alcohol 70% v/v. Purpose: Antiseptic

PURPOSE

Antiseptic, Hand Sanitizer

INDICATIONS AND USAGE

Hand Sanitizer to help reduce bacteria that potentially can cause disease. For use when soap and water are not available.

WARNINGS

For external use only. Flammable. Keep away from heat or flame.

DO NOT USE

- on children less than 2 months of age
- on open skin wounds

When using this product keep out of eyes, ears, and mouth. In case of contact with eyes, rinse eyes thoroughly with water.

Stop use and ask a doctor if irritation or rash occurs. These may be signs of a serious condition.

Keep out of reach of children. If swallowed, get medical help or contact a Poison Control Center right away.

DOSAGE AND ADMINISTRATION

- Place enough product on hands to cover all surfaces. Rub hands together until dry.
- Supervise children under 6 years of age when using this product to avoid swallowing.

STORAGE AND HANDLING

- Store between 15-30C (59-86F)
- Avoid freezing and excessive heat abouve 40C (104F)

INACTIVE INGREDIENT

liquid preneutralized thickener/emulsifier, citric acid, glycerin, water